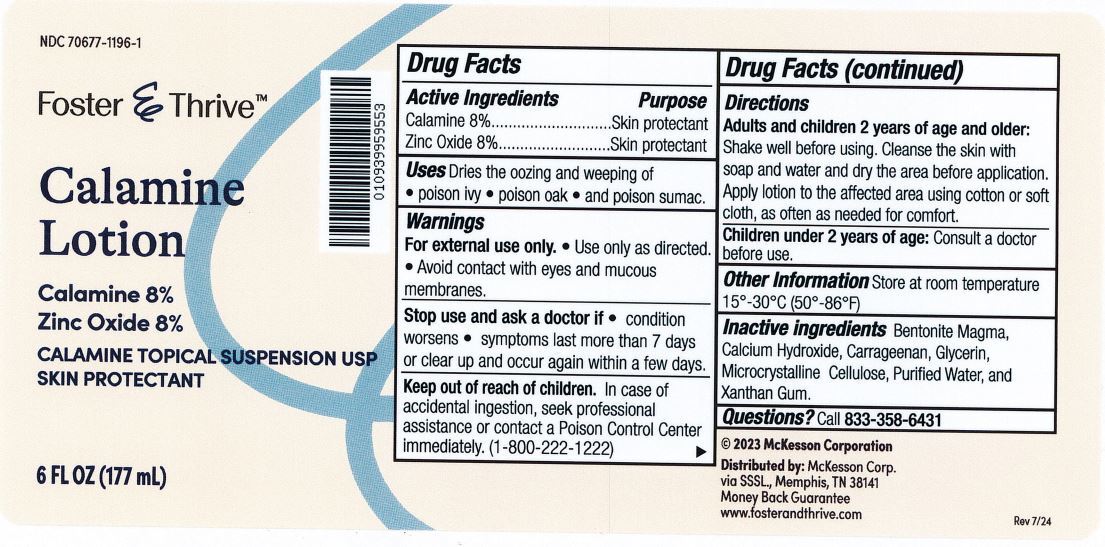 DRUG LABEL: Calamine
NDC: 70677-1196 | Form: LOTION
Manufacturer: Strategic Sourcing Services, LLC
Category: otc | Type: HUMAN OTC DRUG LABEL
Date: 20240914

ACTIVE INGREDIENTS: FERRIC OXIDE RED 80 mg/1 mL; ZINC OXIDE 80 mg/1 mL
INACTIVE INGREDIENTS: BENTONITE; CARRAGEENAN; XANTHAN GUM; CALCIUM HYDROXIDE; GLYCERIN; WATER; MICROCRYSTALLINE CELLULOSE

Foster & Thrive Calamine Lotion

Drug Facts

Active Ingredients

Calamine 8% and Zinc Oxide 8%

Uses

Dries the oozing and weeping of poison ivy, poison oak, and poison sumac.

Purpose

Skin protectant

Warnings

For external use only. Use only as directed.

Avoid contact with eyes and mucous membranes.

Ask a doctor before using on chilren under 2 years of age.

Stop use and ask a doctor if

condition worsens, does not improve or if symptoms last more than 7 days, or clear up and occur again within a few days.

Keep out of reach of children

In case of accidental ingestion, seek professional assistance or contact a Poison Control Center (1-800-222-1222) right away.

Directions

Adults and chidren 2 years of age and older: shake well before using. Cleanse the skin with soap and water and let it dry befroe each use. Apply lotion to the affected area using a cotton or soft cloth, not more than 3 to 4 times daily as needed for comfort.

Children under 2 years of age: Consult a doctor before use

Other information

Store at room temperature 15-30C (59-86F)

Inactive ingredients

Avicel, Bentonite Magma, Calcium Hydroxide, Glycerin, Purified Water, and Xanthan Gum

Questions

Questions? 833-358-6431